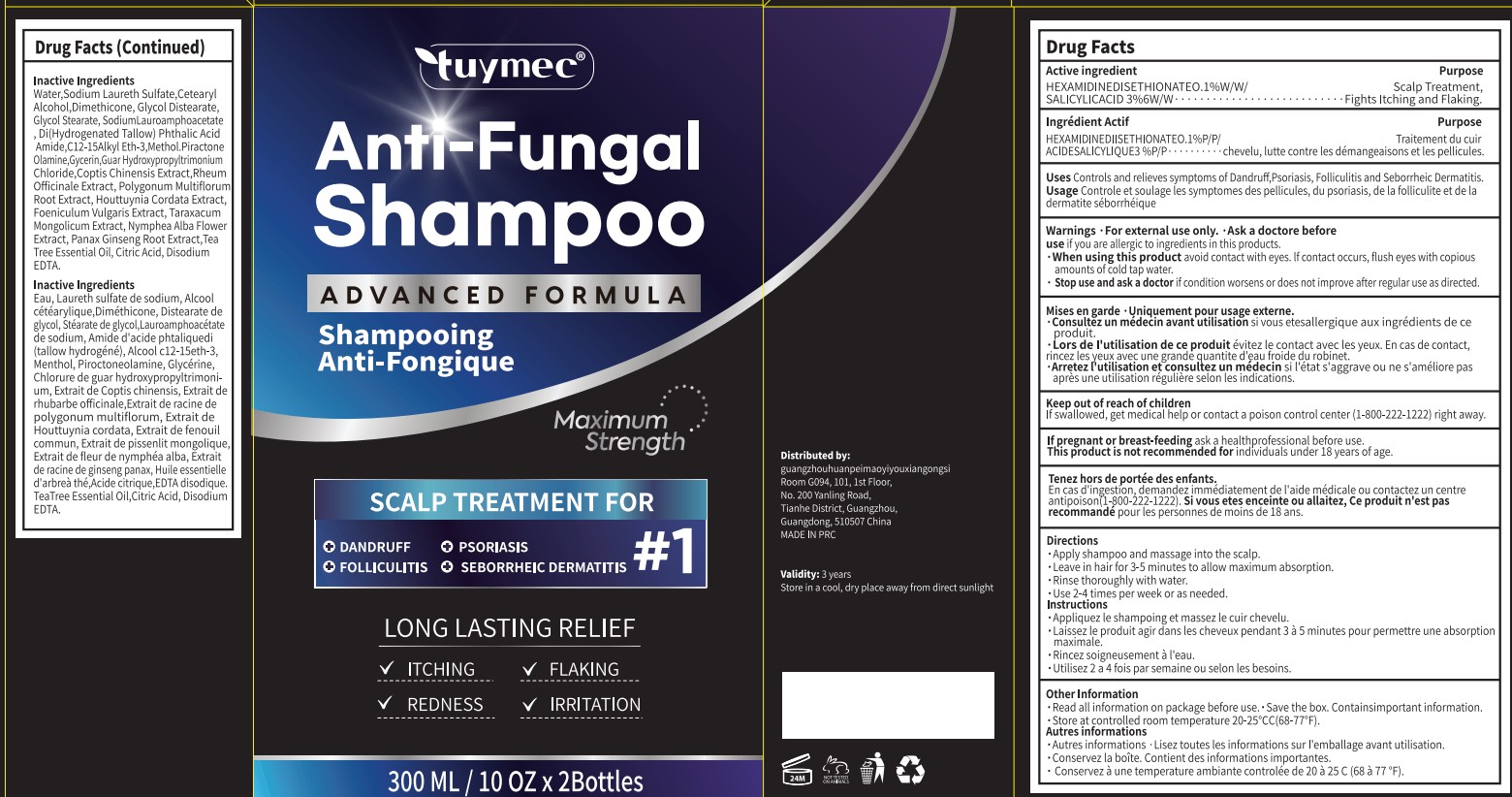 DRUG LABEL: Tuymec Anti-Dandruff Shampoo.
NDC: 87408-005 | Form: SHAMPOO
Manufacturer: Guangzhou Jingliang Cosmetics Co., Ltd.
Category: otc | Type: HUMAN OTC DRUG LABEL
Date: 20260215

ACTIVE INGREDIENTS: SALICYLIC ACID 3 g/100 mL
INACTIVE INGREDIENTS: COPTIS CHINENSIS ROOT; FOENICULUM VULGARE WHOLE; NYMPHAEA ALBA FLOWER; PANAX GINSENG ROOT OIL; PIROCTONE OLAMINE; HOUTTUYNIA CORDATA WHOLE; HEXAMIDINE DIISETHIONATE; WATER; SODIUM LAURETH SULFATE; CETEARYL ALCOHOL; DIMETHICONE; GLYCERIN; CITRIC ACID; MAGNESIUM DISODIUM EDTA; ECULIZUMAB; POLYGONUM BISTORTA ROOT; SODIUM LAUROAMPHOACETATE; TARAXACUM MONGOLICUM; GUAR HYDROXYPROPYLTRIMONIUM CHLORIDE; RHEUM OFFICINALE ROOT; DIHYDROGENATED TALLOW PHTHALIC ACID AMIDE; TEA TREE OIL; C12-15 PARETH-3; MENTHOL; GLYCOL STEARATE

Active Ingredient

SALICYLIC ACID 3%

Ask a doctore before use

If pregnant or breast-feeding ask a health professional before use.

Keep Oot Of Reach Of Children

If swallowed, get medical help or contact a poison control center (1-800-222-1222) right away.

Purpose

Scalp treatment, fights itching and flaking.

Stop Use

Stop use and ask a doctor if condition worsens or does not improve after regular use as directed.

When Using

When using this product avoid contact with eyes. If contact occurs, flush eyes with copious amounts of cold tap water.

Inactive ingredients

Water, Sodium Laureth Sulfate, Cetearyl Alcohol, Dimethicone, Glycol Distearate, Glycol Stearate, Sodium Lauroamphoacetate, Di(Hydrogenated Tallow) Phthalic Acid Amide, C12-15 Alkyl Eth-3, Menthol, Piroctone Olamine, Glycerin, Guar Hydroxypropyltrimonium Chloride, Coptis Chinensis Extract, Rheum Officinale Extract, Polygonum Multiflorum Root Extract, Houttuynia Cordata Extract, Foeniculum Vulgaris Extract, Taraxacum Mongolicum Extract, Nymphea Alba Flower Extract, Panax Ginseng Root Extract, Tea Tree Essential Oil, Citric Acid, Disodium EDTA.

Directions

■ Apply shampoo and massage into the scalp.

■ Leave in hair for 3-5 minutes to allow maximum absorption.

■ Rinse thoroughly with water.

■ Use 2-4 times per week or as needed.

Warnings

For external use only.

Uses

Controls and relives symptoms of Dandruff, Psoriasis, Folliculitis and Seborrheic Dermatitis.

Do Not Use

This product is not recommended for individuals under 18 years of age.

PACKAGE LABEL

Brand: Tuymec

Name: Anti-Dandruff Shampoo

Size: 300 ML/ 10 OZ x 2 Bottles